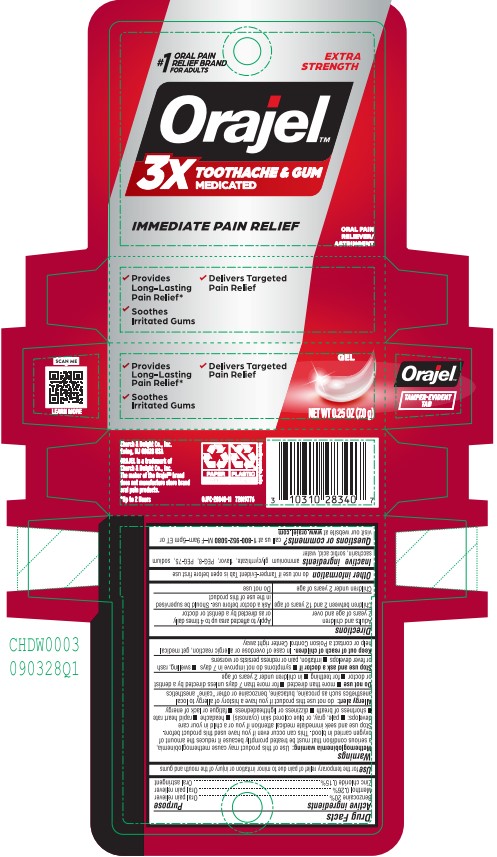 DRUG LABEL: Orajel 3X Medicated For Toothache and Gum
NDC: 10237-790 | Form: GEL
Manufacturer: Church & Dwight Co., Inc.
Category: otc | Type: HUMAN OTC DRUG LABEL
Date: 20251212

ACTIVE INGREDIENTS: MENTHOL 2.6 mg/1 g; BENZOCAINE 200 mg/1 g; ZINC CHLORIDE 1.5 mg/1 g
INACTIVE INGREDIENTS: WATER; POLYETHYLENE GLYCOL 400; METHYL SALICYLATE; SACCHARIN SODIUM; AMMONIUM GLYCYRRHIZATE; PEG-75 LANOLIN; SORBIC ACID

Orajel 3X Medicated For Toothache and Gum, Gel

ACTIVE INGREDIENT

Benzocaine 20%

Menthol 0.26%

Zinc chloride 0.15%

PURPOSE

Oral pain reliever and Oral astringent

Use

for the temporary relief of pain due to minor irritation or injury of the mouth and gums

WARNINGS

Methemoglobinemia warning: use of this product may cause methemoglobinemia, a serious condition that must be treated promptly because it reduces the amount of oxygen carried in blood. This can occur even if you have used this product before. Stop use and seek immediate medical attention if you or a child in your care develops: pale, gray, or blue colored skin (cyanosis), headache, rapid heart rate, shortness of breath, dizziness or lightheadedness, fatigue or lack of energy

Allergy alert: do not use this product if you have a history of allergy to local anesthetics such as procaine, butacaine, benzocaine or other "caine" anesthetics

DO NOT USE

- more than directed
- for more than 7 days unless directed by a dentist or doctor
- for teething
- in children under 2 years of age

Stop use and ask a doctor if

- symptoms do not improve in 7 days
- swelling, rash or fever develops
- irritation, pain or redness persists or worsens

KEEP OUT OF REACH OF CHILDREN

In case of overdose or allergic reaction, get medical help or contact a Poison Control Center right away

Directions

Adults and children 2 years of age and over | Apply to affected area up to 4 times daily or as directed by a dentist or doctor
Children between 2 and 12 years of age | Ask a doctor before use. Should be supervised in the use of this product
Children under 2 years of age | Do not use

Other information

do not use if Tamper-Evident Tab is open before first use

INACTIVE INGREDIENT

ammonium glycyrrhizate, flavor, PEG-8, PEG-75, sodium saccharin, sorbic acid, water

Questions or comments?

call us at 1-800-952-5080 M-F 9am-5pm ET or visit our website at www.orajel.com

PACKAGE LABEL

#1 ORAL PAIN

RELIEF BRAND

FOR ADULTS

EXTRA
STRENGTH

Orajel™

3X TOOTHACHE & GUM

MEDICATED

IMMEDIATE PAIN RELIEF

ORAL PAIN

RELIEVER/

ASTRINGENT

Provides

Long-Lasting

Pain Relief*

Soothes

Irritated Gums

Delivers Targeted

Pain Relief

GEL

NET WT

0.25 OZ (7.0 g)